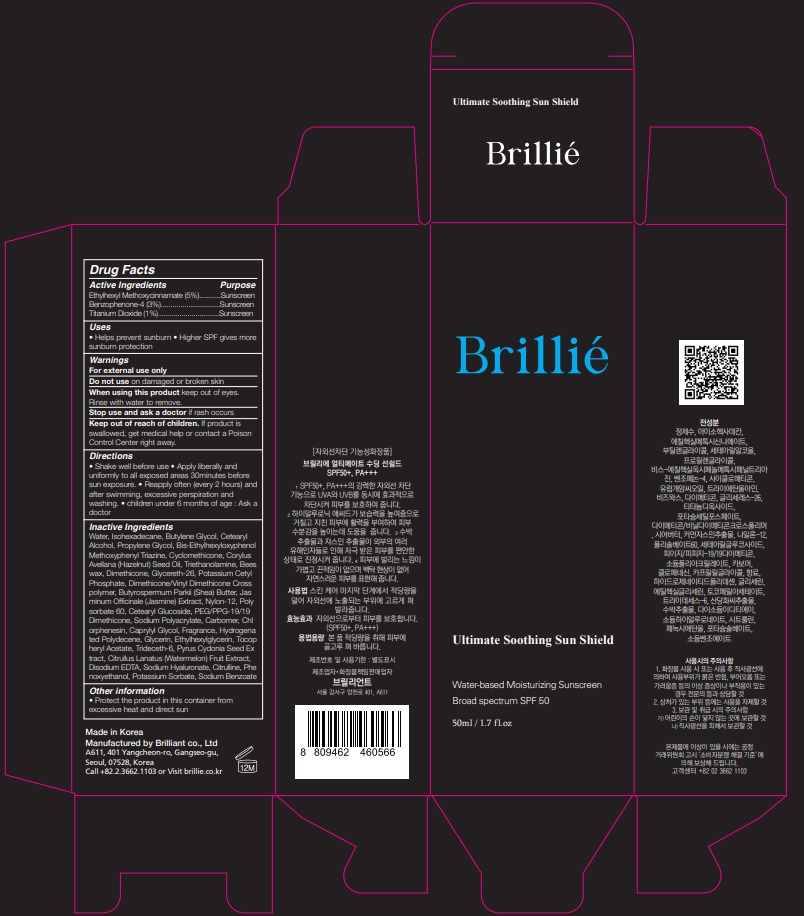 DRUG LABEL: Brillie Ultimate Soothing Sun Shield
NDC: 80134-050 | Form: CREAM
Manufacturer: Inhanzglobal Co.,Ltd
Category: otc | Type: HUMAN OTC DRUG LABEL
Date: 20200821

ACTIVE INGREDIENTS: OCTINOXATE 2.5 g/50 mL; SULISOBENZONE 1.5 g/50 mL
INACTIVE INGREDIENTS: CAPRYLYL GLYCOL; CETEARYL GLUCOSIDE; CHLORPHENESIN; .ALPHA.-TOCOPHEROL ACETATE; TRIDECETH-6; EDETATE DISODIUM; HYALURONATE SODIUM; DIMETHICONE/VINYL DIMETHICONE CROSSPOLYMER (SOFT PARTICLE); SODIUM POLYACRYLATE (8000 MW); CARBOMER HOMOPOLYMER, UNSPECIFIED TYPE; HYDROGENATED POLYDECENE TYPE I; ETHYLHEXYLGLYCERIN; CYDONIA OBLONGA SEED; PHENOXYETHANOL; POTASSIUM SORBATE; SODIUM BENZOATE; WATER; PROPYLENE GLYCOL; DIMETHICONE; SHEA BUTTER; JASMINUM OFFICINALE FLOWER; TITANIUM DIOXIDE 0.5 g/50 mL; CETOSTEARYL ALCOHOL; BEMOTRIZINOL; CYCLOMETHICONE; TROLAMINE; YELLOW WAX; ISOHEXADECANE; BUTYLENE GLYCOL; EUROPEAN HAZELNUT OIL; GLYCERETH-26; POTASSIUM CETYL PHOSPHATE; NYLON-12; POLYSORBATE 60; PEG/PPG-19/19 DIMETHICONE; GLYCERIN; WATERMELON; CITRULLINE

Brillié Ultimate Soothing Sun Shield